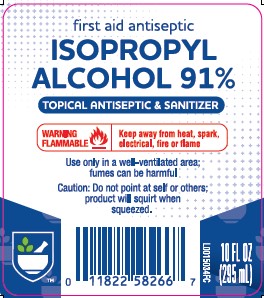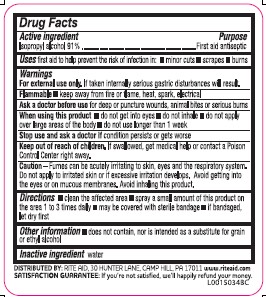 DRUG LABEL: Isopropyl Alcohol
NDC: 11822-5826 | Form: LIQUID
Manufacturer: Rite Aid Corporation
Category: otc | Type: HUMAN OTC DRUG LABEL
Date: 20260130

ACTIVE INGREDIENTS: ISOPROPYL ALCOHOL 0.91 mg/1 mL
INACTIVE INGREDIENTS: WATER

Rite Aid 804.003/804AA
91% Isopropyl Alcohol

Active Ingredient

Isopropyl alcohol 91%

Purpose

First aid antiseptic

Uses

first aid to help prevent the risk of infection in:

- minor cuts
- scrapes
- burns

Warnings

For external use only.If taken internally serious gastric disturbances will result.

Flammable

- Keep away from fire or flame, heat, spark, electrical

Ask a doctor before use

for deep or puncture wounds, animal bites or serious burns

When using this product

- do not get into eyes
- do not inhale
- do not apply over large areas of the body
- do not use longer than 1 week

Stop use and ask a doctor if

condition persists or gets worse

Keep out of reach of children.

If swallowed, get medical help or contact a Poison Control Center right away.

Caution

Fumes can be acutely irritating to skin, eyes and respiratory system. Do not apply to irritated skin or if excessive irritation develops. Avoid getting into the eyes or on mucous membranes. Avoid inhaling this product.

Directions

- clean the affected area
- spray a small amount of this product on the area 1 to 3 times daily
- may be covered with a sterile bandage
- if bandaged, let dry first

other information

- does not contain, nor is intended as a substitute for grain or ethyl alcohol

Inactive ingredient

water

ADVERSE REACTION

DISTRIBUTED BY: RITE AID, 30 HUNTER LANE, CAMP HILL, PA 17011 www.riteaid.com

SATISFACTION GUARANTEE: IF YOU'RE NOT SATISFIED, WE'LL HAPPILY REFUND YOUR MONEY.

principal display panel

first aid antiseptic

isopropyl alcohol 91%

topical antiseptic & sanitzer

WARNING FLAMMABLE - Keep away from heat, spark, electrical, fire or flame

USE ONLY IN A WELL-VENTILATED AREA; FUMES MAY BE HARMFUL

CAUTION: DO NOT POINT AT SELF OR OTHERS; PRODUCT WILL SQUIRT WHEN SQUEEZED

10 FL OZ (295 mL)